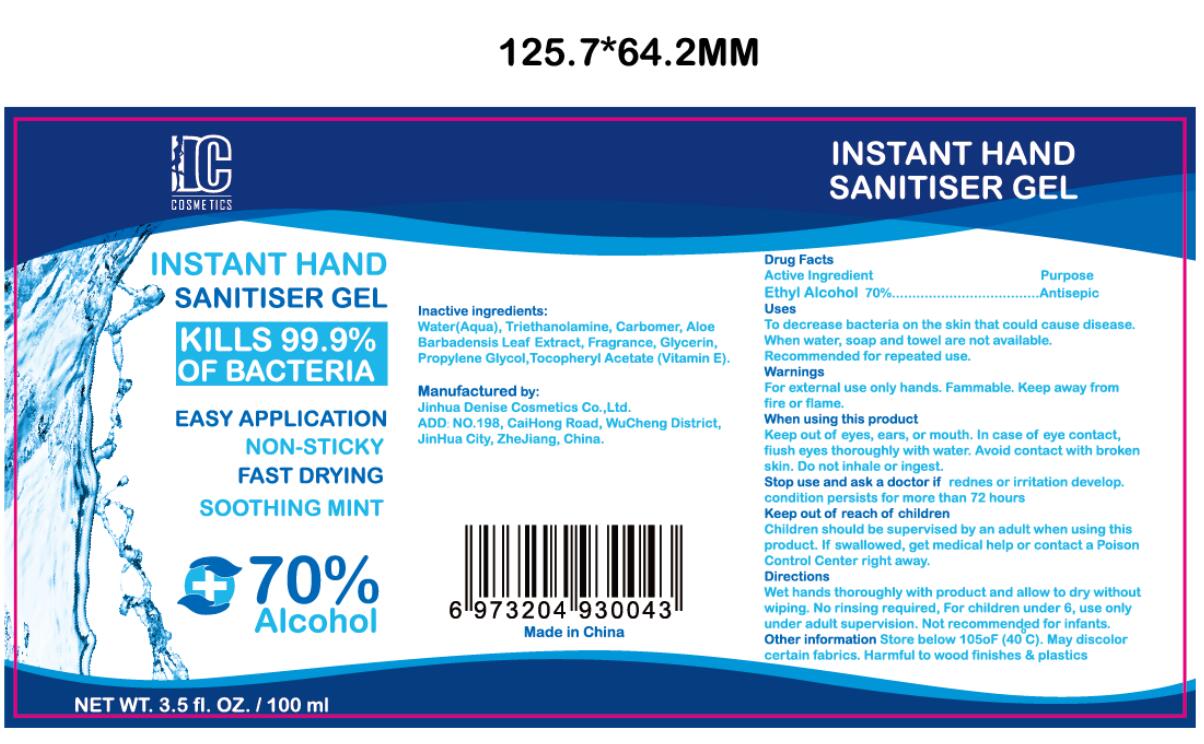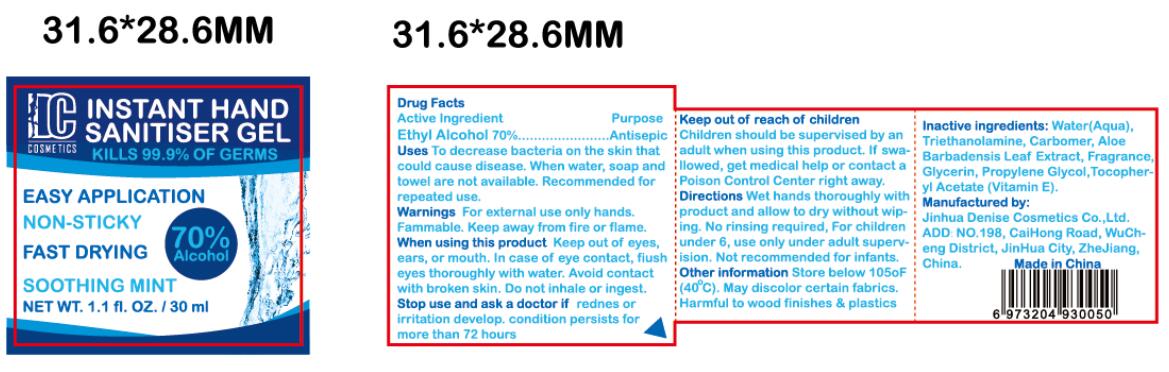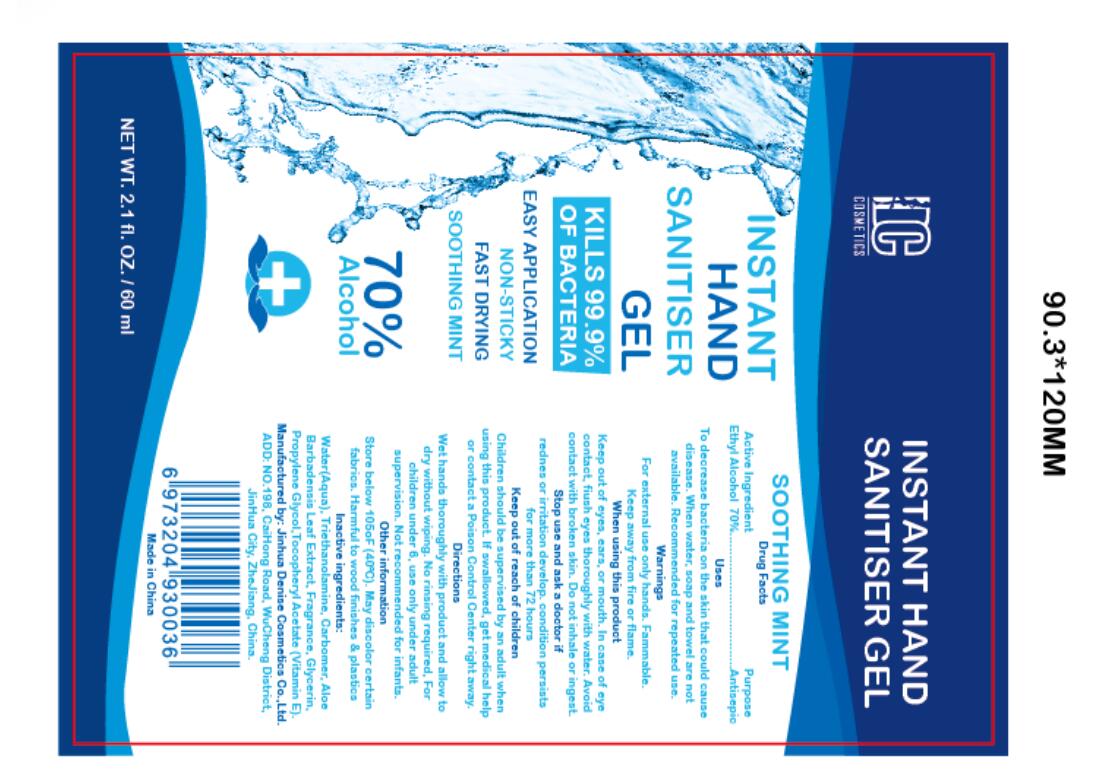 DRUG LABEL: INSTANT HAND SANITISER
NDC: 77663-006 | Form: GEL
Manufacturer: JinHua Denise Cosmetics CO., LTD.
Category: otc | Type: HUMAN OTC DRUG LABEL
Date: 20200523

ACTIVE INGREDIENTS: ALCOHOL 70 mL/100 mL
INACTIVE INGREDIENTS: .ALPHA.-TOCOPHEROL ACETATE; GLYCERIN; TROLAMINE; WATER; CARBOMER HOMOPOLYMER, UNSPECIFIED TYPE; ALOE VERA LEAF; PROPYLENE GLYCOL; FRAGRANCE LAVENDER & CHIA F-153480

INSTANT HAND SANITISER GEL

Active Ingredient(s)

Ethyl Alcohol 70%

Purpose

Antisepic

Use

To decrease bacteria on the skin that could cause disease. When water, soap and towel are not available. Recommended for repeated use.

Warnings

For external use only hands. Fammable. Keep away from fire or flame.When using this product Keep out of eyes, ears, or mouth. In case of eye
contact, fiush eyes thoroughly with water. Avoid contact with broken skin. Do not inhale or ingest.
Stop use and ask a doctor if rednes or irritation develop. condition persists for more than 72 hours.
Keep out of reach of children
Children should be supervised by an adult when using this product. If swallowed, get medical help or contact a Poison Control Center right away.

Do not use

Do not inhale or ingest

When using this product Keep out of eyes, ears, or mouth. In case of eye
contact, fiush eyes thoroughly with water. Avoid contact with broken skin.

Stop use and ask a doctor if rednes or irritation develop. condition persists for more than 72 hours.

Keep out of reach of children
Children should be supervised by an adult when using this product. If swallowed, get medical help or contact a Poison Control Center right away.

Directions

Wet hands thoroughly with product and allow to dry without wiping. No rinsing required, For children under 6, use only under adult supervision. Not recommended for infants.

Other information

Store below 105°F (40 °C). May discolor certain fabrics. Harmful to wood finishes & plastics

Inactive ingredients

Water(Aqua), Triethanolamine, Carbomer, Aloe
Barbadensis Leaf Extract, Fragrance, Glycerin, Propylene Glycol,Tocopheryl Acetate (Vitamin E).